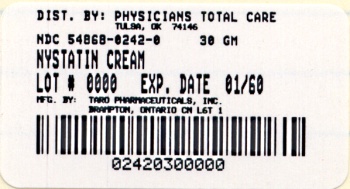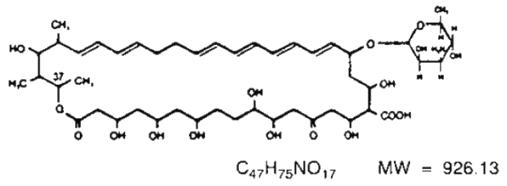 DRUG LABEL: NYSTATIN
NDC: 54868-0242 | Form: CREAM
Manufacturer: Physicians Total Care, Inc.
Category: prescription | Type: HUMAN PRESCRIPTION DRUG LABEL
Date: 20110510

ACTIVE INGREDIENTS: NYSTATIN 100000 [USP'U]/1 g
INACTIVE INGREDIENTS: ALGELDRATE; CETEARETH-15; METHYLPARABEN; GLYCERYL MONOSTEARATE; PROPYLENE GLYCOL; PROPYLPARABEN; WATER; SODIUM HYDROXIDE; SORBITOL; TITANIUM DIOXIDE; PETROLATUM

Rx only

DESCRIPTION

Nystatin Cream is for dermatologic use.

Nystatin is a polyene antimycotic obtained from Streptomyces noursei. It is a yellow to light tan powder with a cereal-like odor, very soluble in water, and slightly to sparingly soluble in alcohol. Structural formula:

Nystatin Cream contains the antifungal antibiotic nystatin at a concentration of 100,000 USP Nystatin Units per gram in an aqueous, perfumed cream base containing purified water, propylene glycol, methylparaben, propylparaben, white petrolatum, glyceryl monostearate, polyethylene glycol 400 monostearate, ceteareth-15, medical antifoam AF emulsion, aluminum hydroxide gel, titanium dioxide, sorbitol solution, and, if necessary, sodium hydroxide for pH adjustment.

CLINICAL PHARMACOLOGY

Nystatin is an antifungal antibiotic which is both fungistatic and fungicidal in vitro against a wide variety of yeasts and yeast-like fungi. It probably acts by binding to sterols in the cell membrane of the fungus with a resultant change in membrane permeability allowing leakage of intracellular components. Nystatin is the first well tolerated antifungal antibiotic of dependable efficacy for the treatment of cutaneous, oral and intestinal infections caused by Candida (Monilia) albicans and other Candida species. It exhibits no appreciable activity against bacteria.

Nystatin provides specific therapy for all localized forms of candidiasis. Symptomatic relief is rapid, often occurring within 24 to 72 hours after the initiation of treatment. Cure is effected both clinically and mycologically in most cases of localized candidiasis.

INDICATIONS AND USAGE

Nystatin Cream is indicated in the treatment of cutaneous or mucocutaneous mycotic infections caused by Candida (Monilia) albicans and other Candida species.

CONTRAINDICATIONS

Nystatin Cream is contraindicated in patients with a history of hypersensitivity to any of its components.

PRECAUTIONS

Should a reaction of hypersensitivity occur the drug should be immediately withdrawn and appropriate measures taken.

Nystatin Cream is not for ophthalmic use.

ADVERSE REACTIONS

Nystatin is virtually nontoxic and nonsensitizing and is well tolerated by all age groups including debilitated infants, even on prolonged administration. If irritation on topical application should occur, discontinue medication.

DOSAGE AND ADMINISTRATION

Nystatin Cream should be applied liberally to affected areas twice daily or as indicated until healing is complete.

Nystatin Cream is usually preferred to Nystatin Ointment in candidiasis involving intertriginous areas; very moist lesions, however, are best treated with Nystatin Topical Powder.

HOW SUPPLIED

Nystatin Cream is a smooth yellow cream with a characteristic perfume odor.

Nystatin Cream is providing 100,000 USP Nystatin Units per gram in

15 gram tubes | NDC 54868-0242-1
30 gram tubes | NDC 54868-0242-0

Store at 20°-25°C (68°-77°F) [see USP Controlled Room Temperature].

Mfd. by: Taro Pharmaceuticals Inc.
Brampton, Ontario, Canada L6T 1C1

Dist. by: Taro Pharmaceuticals U.S.A., Inc.
Hawthorne, NY 10532

Revised: June, 2005

PK-1161-3 262

Relabeling of "Additional" label by:
Physicians Total Care, Inc.
Tulsa, OK 74146

PRINCIPAL DISPLAY PANEL

Nystatin Cream